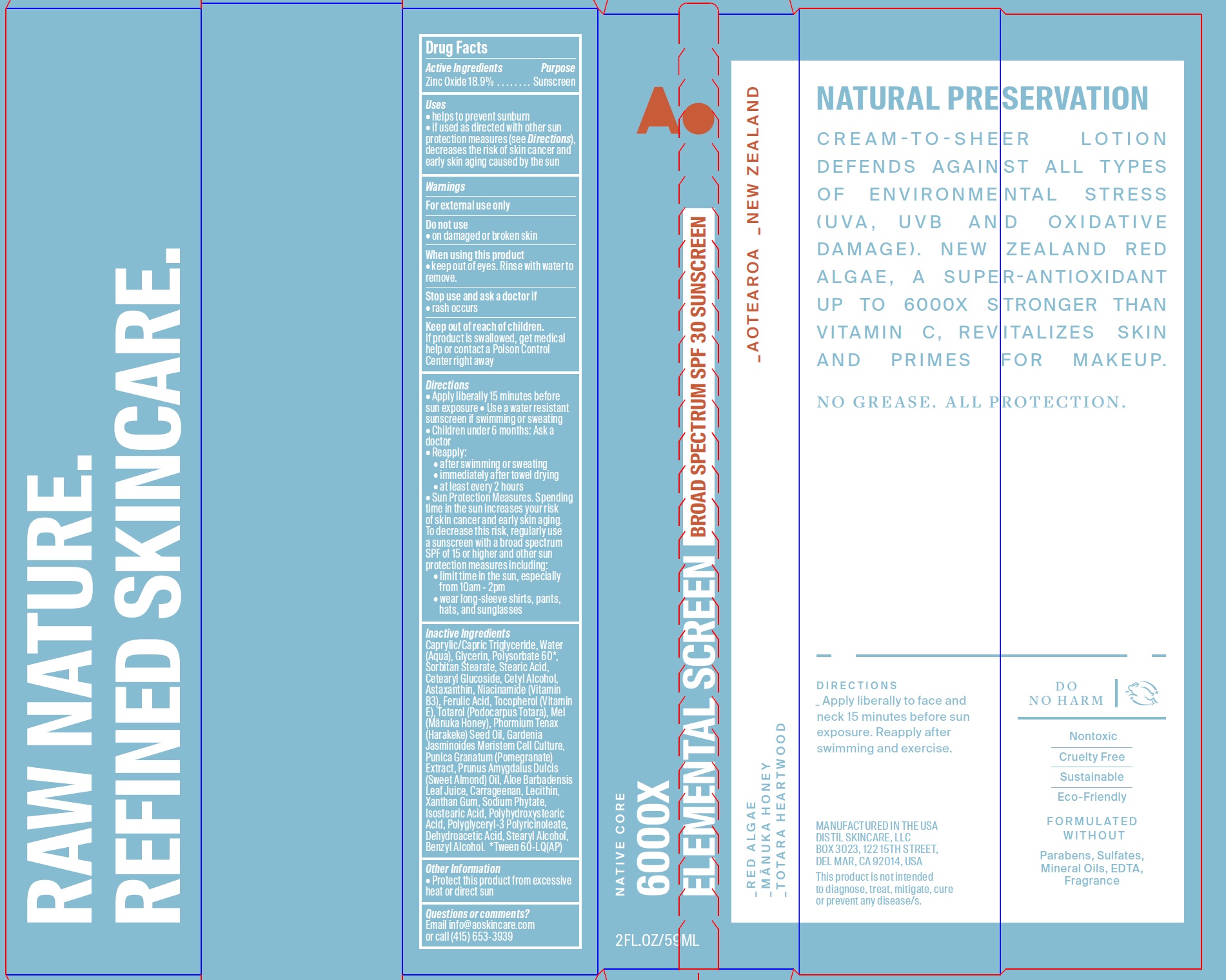 DRUG LABEL: 6000X Elemental Screen Broad Spectrum SPF30 Sunscreen
NDC: 62742-4200 | Form: CREAM
Manufacturer: Allure Labs Inc
Category: otc | Type: HUMAN OTC DRUG LABEL
Date: 20210208

ACTIVE INGREDIENTS: ZINC OXIDE 189 mg/1 g
INACTIVE INGREDIENTS: WATER; GLYCERIN; POLYSORBATE 60; SORBITAN MONOSTEARATE; MEDIUM-CHAIN TRIGLYCERIDES; FERULIC ACID; PHORMIUM TENAX SEED OIL; POLYHYDROXYSTEARIC ACID (2300 MW); POLYGLYCERYL-3 PENTARICINOLEATE; PUNICA GRANATUM ROOT BARK; ALOE VERA LEAF; CETEARYL GLUCOSIDE; HONEY; GARDENIA JASMINOIDES WHOLE; CARRAGEENAN; STEARYL ALCOHOL; CETYL ALCOHOL; ASTAXANTHIN; NIACINAMIDE; .ALPHA.-TOCOPHEROL; TOTAROL; ALMOND OIL; XANTHAN GUM; DEHYDROACETIC ACID; STEARIC ACID; ISOSTEARIC ACID; BENZYL ALCOHOL; LECITHIN, SOYBEAN; PHYTATE SODIUM

Drug Facts

Active Ingredients
Zinc Oxide 18.9%

Purpose
Sunscreen

Uses
• helps to prevent sunburn
• if used as directed with other sun protection measures (see Directions), decreases the risk of skin cancer and early skin aging caused by the sun

Warnings
For external use only

Do not use
• on damaged or broken skin

When using this product
• keep out of eyes. Rinse with water to remove.

Stop use and ask a doctor if
• rash occurs

KEEP OUT OF REACH OF CHILDREN

If product is swallowed, get medical help or contact a Poison Control Center right away

Directions
• Apply liberally 15 minutes before sun exposure • Use a water resistant sunscreen if swimming or sweating
• Children under 6 months: Ask a doctor
Reapply:

• after swimming or sweating
• immediately after towel drying
• at least every 2 hours
• Sun Protection Measures. Spending time in the sun increases your risk of skin cancer and early skin aging. To decrease this risk, regularly use a sunscreen with a broad spectrum SPF of 15 or higher and other sun protection measures including:
• limit time in the sun, especially from 10am - 2pm
• wear long-sleeve shirts, pants, hats, and sunglasses

Inactive Ingredients
Caprylic/Capric Triglyceride, Water(Aqua), Glycerin, Polysorbate 60*, Sorbitan Stearate, Stearic Acid,Cetearyl Glucoside, Cetyl Alcohol, Astaxanthin, Niacinamide (Vitamin B3), Ferulic Acid, Tocopherol (Vitamin E), Totarol (Podocarpus Totara), Mel (Manuka Honey), Phormium Tenax (Harakeke) Seed Oil, Gardenia Jasminoides Meristem Cell Culture, Punica Granatum (Pomegranate)
Extract, Prunus Amygdalus Dulcis (Sweet Almond) Oil, Aloe Barbadensis Leaf Juice, Carrageenan, Lecithin, Xanthan Gum, Sodium Phytate, Isostearic Acid, Polyhydroxystearic Acid, Polyglyceryl-3 Polyricinoleate, Dehydroacetic Acid, Stearyl Alcohol, Benzyl Alcohol. *Tween 60-LQ(AP)

Other Information
• Protect this product from excessive heat or direct sun

Questions or comments?
Email info@aoskincare.com
or call (415) 653-3939

PACKAGE LABEL

MANUFACTURED IN THE USA
DISTIL SKINCARE, LLC
BOX 3023, 122 15TH STREET,
DEL MAR, CA 92104, USA